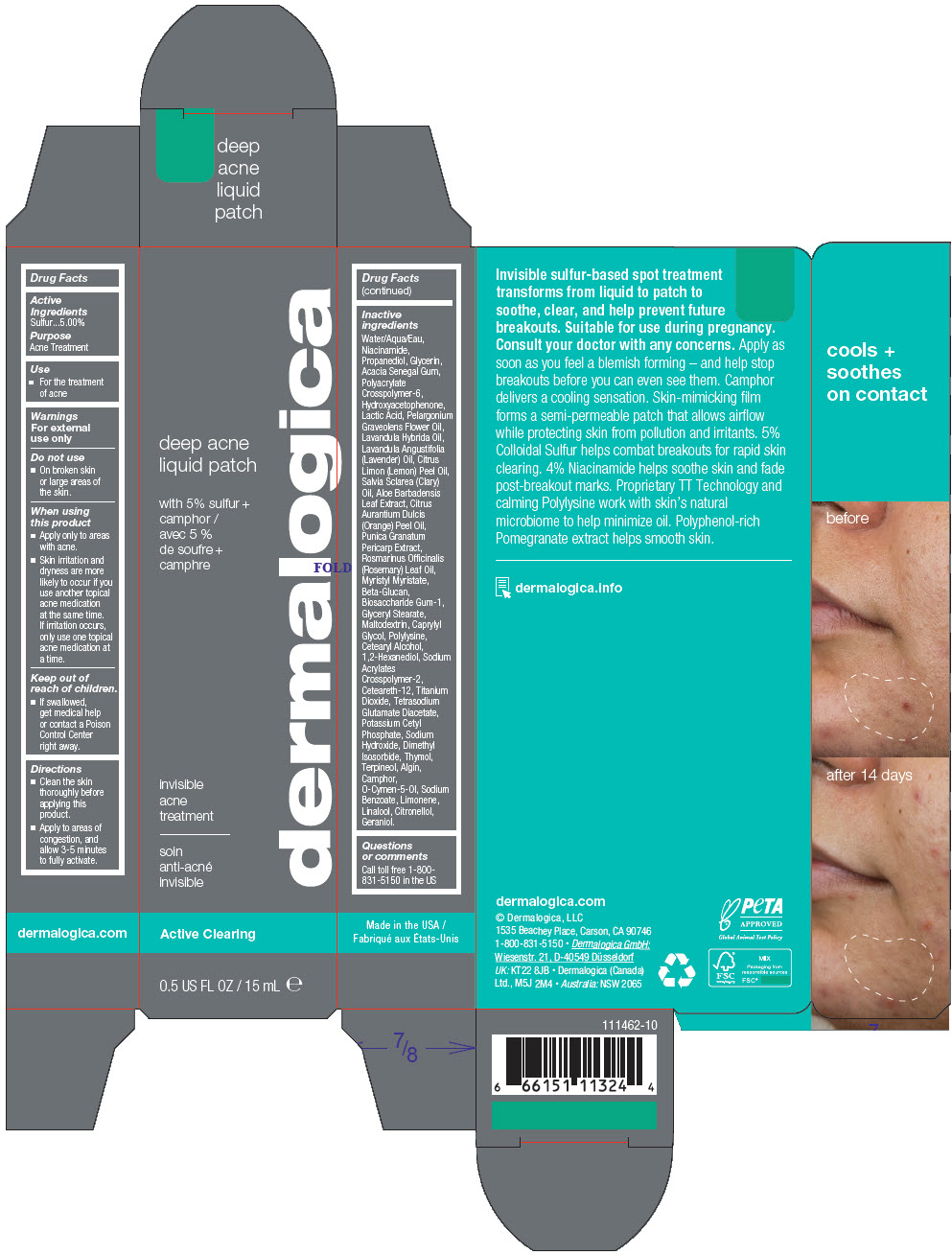 DRUG LABEL: DEEP ACNE
NDC: 68479-240 | Form: GEL
Manufacturer: Dermalogica, LLC.
Category: otc | Type: HUMAN OTC DRUG LABEL
Date: 20241226

ACTIVE INGREDIENTS: Sulfur 5 mg/100 mL
INACTIVE INGREDIENTS: Water; Niacinamide; Propanediol; Glycerin; ACACIA; AMMONIUM ACRYLOYLDIMETHYLTAURATE, DIMETHYLACRYLAMIDE, LAURYL METHACRYLATE AND LAURETH-4 METHACRYLATE COPOLYMER, TRIMETHYLOLPROPANE TRIACRYLATE CROSSLINKED (45000 MPA.S); Myristyl Myristate; Maltodextrin; Dimethyl Isosorbide; Sodium Acrylates Crosspolymer-2; Hydroxyacetophenone; Ceteareth-12; LACTIC ACID, DL-; GLYCERYL MONOSTEARATE; ALOE VERA LEAF; o-Cymen-5-ol; Titanium Dioxide; Tetrasodium Glutamate Diacetate; ORANGE OIL, COLD PRESSED; Pelargonium Graveolens Flower Oil; SODIUM ALGINATE; Terpineol; Thymol; POMEGRANATE FRUIT RIND; LAVENDER OIL; LAVANDIN OIL; Sodium Benzoate; 1,2-Hexanediol; Biosaccharide Gum-1; Caprylyl Glycol; CETOSTEARYL ALCOHOL; Potassium Cetyl Phosphate; CAMPHOR (NATURAL); LEMON OIL, DISTILLED; ROSEMARY OIL; CLARY SAGE OIL; Sodium Hydroxide; LIMONENE, (+)-; LINALOOL, (+/-)-; .BETA.-CITRONELLOL, (R)-; Geraniol

DEEP ACNE LIQUID PATCH

Drug Facts

Active Ingredients

Sulfur...5.00%

Purpose

Acne Treatment

Use

- For the treatment of acne

Warnings

For external use only

Do not use

- On broken skin or large areas of the skin.

When using this product

- Apply only to areas with acne.
- Skin irritation and dryness are more likely to occur if you use another topical acne medication at the same time. If irritation occurs, only use one topical acne medication at a time.

Keep out of reach of children.

- If swallowed, get medical help or contact a Poison Control Center right away.

Directions

- Clean the skin thoroughly before applying this product.
- Apply to areas of congestion, and allow 3-5 minutes to fully activate.

Inactive ingredients

Water/Aqua/Eau, Niacinamide, Propanediol, Glycerin, Acacia Senegal Gum, Polyacrylate Crosspolymer-6, Hydroxyacetophenone, Lactic Acid, Pelargonium Graveolens Flower Oil, Lavandula Hybrida Oil, Lavandula Angustifolia (Lavender) Oil, Citrus Limon (Lemon) Peel Oil, Salvia Sclarea (Clary) Oil, Aloe Barbadensis Leaf Extract, Citrus Aurantium Dulcis (Orange) Peel Oil, Punica Granatum Pericarp Extract, Rosmarinus Officinalis (Rosemary) Leaf Oil, Myristyl Myristate, Beta-Glucan, Biosaccharide Gum-1, Glyceryl Stearate, Maltodextrin, Caprylyl Glycol, Polylysine, Cetearyl Alcohol, 1,2-Hexanediol, Sodium Acrylates Crosspolymer-2, Ceteareth-12, Titanium Dioxide, Tetrasodium Glutamate Diacetate, Potassium Cetyl Phosphate, Sodium Hydroxide, Dimethyl Isosorbide, Thymol, Terpineol, Algin, Camphor, O-Cymen-5-Ol, Sodium Benzoate, Limonene, Linalool, Citronellol, Geraniol.

Questions or comments

Call toll free 1-800-831-5150 in the US

PRINCIPAL DISPLAY PANEL - 15 mL Tube Carton

deep acne
liquid patch

with 5% sulfur +
camphor

invisible
acne
treatment

dermalogica

Active Clearing

0.5 US FL OZ / 15 mL e